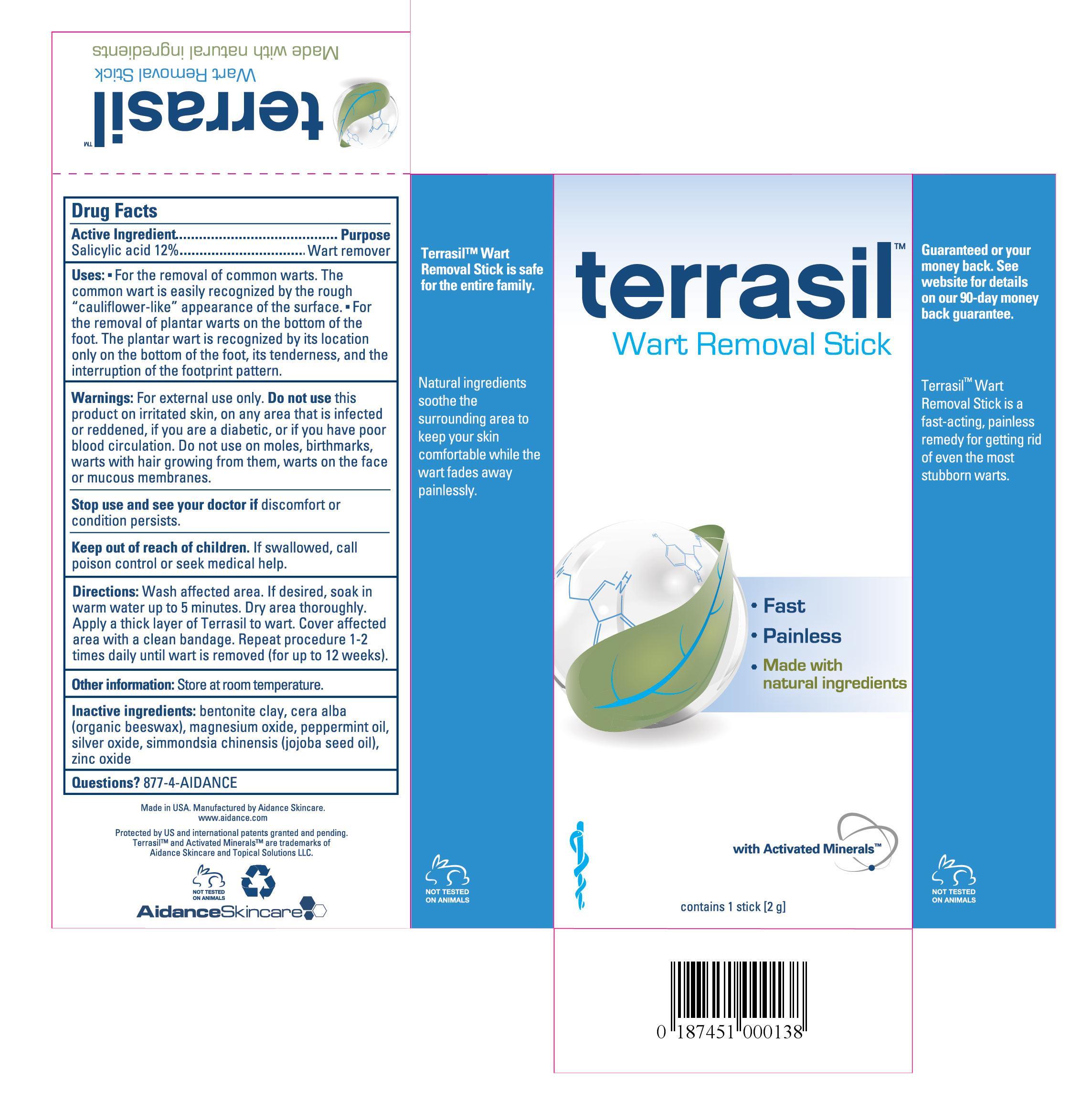 DRUG LABEL: Terrasil Wart Removal
NDC: 24909-111 | Form: STICK
Manufacturer: Aidance Skincare & Topical Solutions, LLC
Category: otc | Type: HUMAN OTC DRUG LABEL
Date: 20120905

ACTIVE INGREDIENTS: SALICYLIC ACID 12.0 g/100 g
INACTIVE INGREDIENTS: BENTONITE; JOJOBA OIL; MAGNESIUM OXIDE; PEPPERMINT OIL; SILVER OXIDE; WHITE WAX; ZINC OXIDE

Drug Facts

Active Ingredient

Salicylic Acid 12%

Purpose

Wart remover

Uses

- For the removal of common warts. The common wart is easily recognized by the rough “cauliflower-like” appearance of the surface.
- For the removal of plantar warts on the bottom of the foot. The plantar wart is recognized by its location only on the bottom of the foot, its tenderness, and the interruption of the footprint pattern.

Warnings

For external use only. Do not use this product on irritated skin, on any area that is infected or reddened, if you are a diabetic, or if you have poor blood circulation. Do not use on moles, birthmarks, warts with hair growing from them, warts on the face or mucous membranes.

Keep out of reach of children.

If swallowed, call poison control or seek medical help.

Stop use and see your doctor if discomfort or condition persists.

Directions

Wash affected area. If desired, soak in warm water up to 5 minutes. Dry area thoroughly. Apply a thick layer of Terrasil to wart. Cover affected area with a clean bandage. Repeat procedure 1-2 times daily until wart is removed (for up to 12 weeks).

Other Information

Store at room temperature.

Inactive Ingredients

bentonite clay, cera alba (organic beeswax), magnesium oxide, peppermint oil, silver oxide, simmondsia chinensis (jojoba seed oil), zinc oxide.

Questions? 877-4-AIDANCE